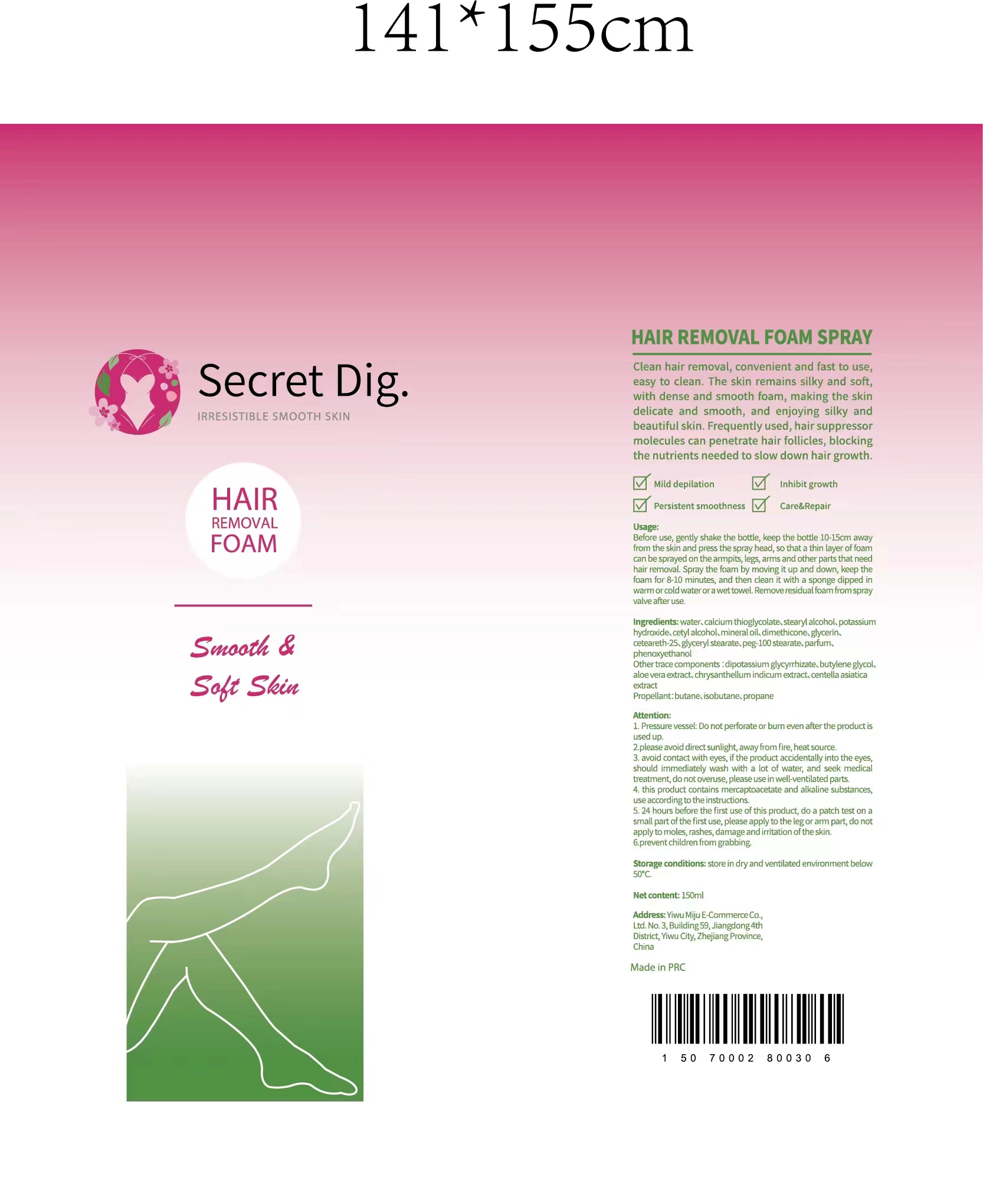 DRUG LABEL: Secret Dig hair removal spray. foam
NDC: 84462-457 | Form: AEROSOL, FOAM
Manufacturer: Yiwu Mijue electronic Commerce Co., LTD
Category: otc | Type: HUMAN OTC DRUG LABEL
Date: 20240709

ACTIVE INGREDIENTS: CALCIUM THIOGLYCOLATE 36 g/100 mL
INACTIVE INGREDIENTS: WATER; BUTYLENE GLYCOL; PARFUMIDINE; PHENOXYETHANOL; STEARYL ALCOHOL; .ALPHA.,.BETA.'-DIGLYCERIN; .ALPHA.-GLUCOSE-1-PHOSPHATE DIPOTASSIUM DIHYDRATE; DIMETHICONE 1000; CETYL ALCOHOL; POTASSIUM HYDROXIDE; ISOPROPYL MYRISTATE; ALOE VERA LEAF; ISOBUTANETHIOL; CETEARETH-10 PHOSPHATE; CHRYSANTHELLUM INDICUM TOP; CENTELLA ASIATICA TRITERPENOIDS; CETEARETH-6 OLIVATE; AMMONIUM GLYCYRRHIZATE PENTAHYDRATE; BUTANE

84462-457 蜜掘电子

ACTIVE INGREDIENT

1.CALCIUM THIOGLYCOLATE:3.2

2.POTASSIUM HYDROXIDE:2.3

PURPOSE

Clean hair removal.convenient and fast to use

INDICATIONS AND USAGE

Clean hair removal,convenient and fast to use,sasy to clean.the skin remains silky and soft,with dense and smooth foam,making the skin delicate and smooth and enjoying silky and beautiful skin.Frequently used,hair suppressor molecules can penetrate hair follicles,blocking the nutrients needed to slow down hair growth.

Usage:

Before use,gently shake the bottle,keep the bottle 10-15cm away from the skin and press the spray head,so that a thin layer of foam can be sprayed on the armpits,legs,arms and other parts that need hair removal

Please keep out of reach of children section

WARNINGS

1.Pressure vessel:Do not perforate or burn even after the product is used up

2.Please avoid direst sunlight,away from fire,heat source

3.avoid contact with eyes,if the product accidentally into the eyes,should immediately wash with a lot of water,and seek medical treatment,do not overuse,please use in well-ventilated parts.

4.this product contains mercaptoacetate and alkaline substances,use according to the instructions.

5.24 hours brfore the first use of this product,do a patch test on a small part of the first use,please apply to the leg or arm part,do not apply to moles,rashes,damage and irritation of the skin.

6.prevent children from grabbing.

INACTIVE INGREDIENT

1.WATER :65

2.STEARYL ALCOHOL:3.2

3.CETYL ALCOHOL:1.3

4.ISOPROPYL MYRISTATE:0.7

5.DIMETHICONE:0.31

6.GLYCERIN:0.15

7.CETEARETH-25:0.16

8.CETEARETH-6:0.15

9.PHENOXYETHANOL:0.13

10.PARFUM:0.14

11.DIPOTASSIUM 12.GLYCYRRHIZATE:0.15

13.ALOE VERA EXTRACT:0.14

14.BUTYLENE GLYCOL:0.15

15.CHRYSANTHELLUM INDICUM EXTRACT PROPANE:0.13

16.CENTELLA ASIATICA EXTRACT:0.14

17.BUTANE:13

18.ISOBUTANE:11

DOSAGE AND ADMINISTRATION

Store in dry and ventilated environment below 50 degrees

Net content:150ml